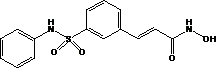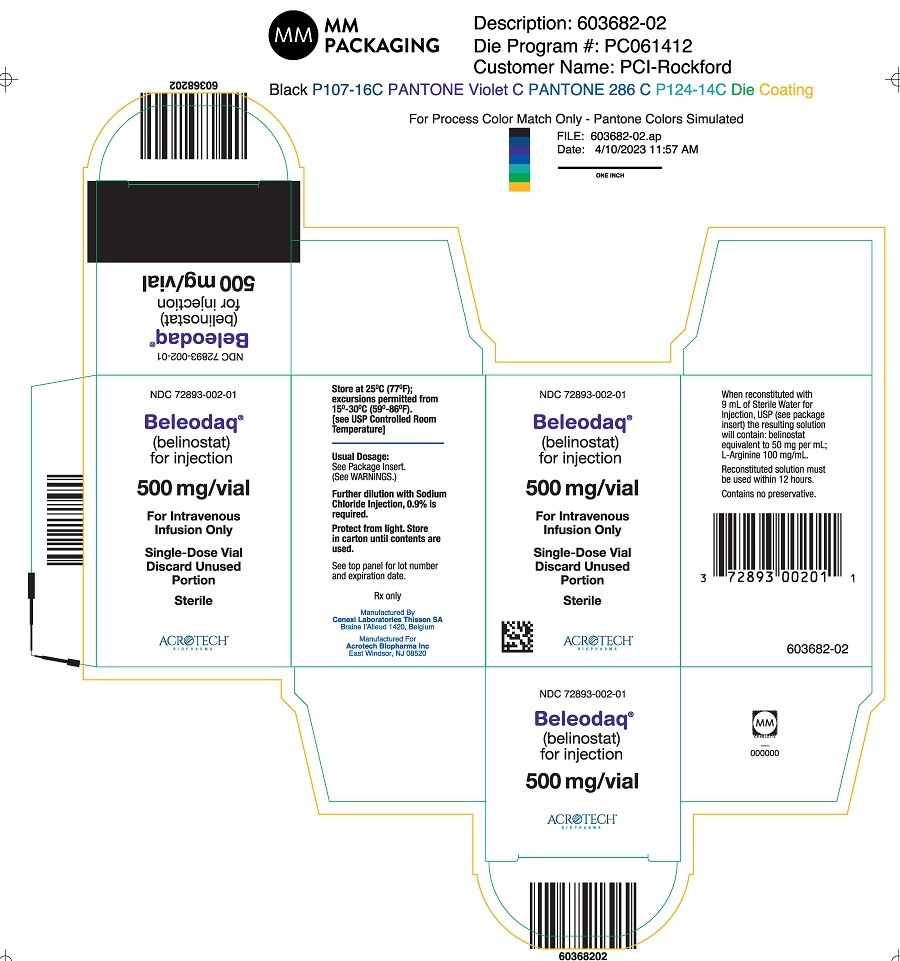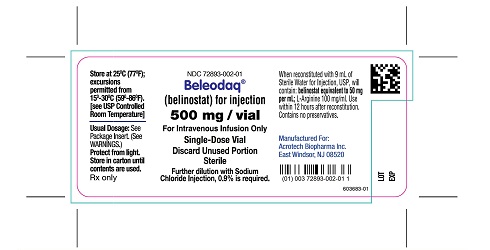 DRUG LABEL: Beleodaq
NDC: 72893-002 | Form: INJECTION, POWDER, LYOPHILIZED, FOR SOLUTION
Manufacturer: Acrotech Biopharma Inc
Category: prescription | Type: Human Prescription Drug Label
Date: 20250407

ACTIVE INGREDIENTS: BELINOSTAT 500 mg/10 mL
INACTIVE INGREDIENTS: ARGININE 1000 mg/10 mL

HIGHLIGHTS OF PRESCRIBING INFORMATION

These highlights do not include all the information needed to use BELEODAQ safely and effectively. See full prescribing information for BELEODAQ.
BELEODAQ® (belinostat) for injection, for intravenous use
Initial U.S. Approval: 2014

RECENT MAJOR CHANGES

Dosage and Administration (2.3, 2.4, 2.6) 11/2024

1 INDICATIONS AND USAGE

Beleodaq is a histone deacetylase inhibitor indicated for the treatment of adult patients with relapsed or refractory peripheral T-cell lymphoma (PTCL).

This indication is approved under accelerated approval based on tumor response rate and duration of response. An improvement in survival or disease-related symptoms has not been established. Continued approval for this indication may be contingent upon verification and description of clinical benefit in the confirmatory trial.(1)

2 DOSAGE AND ADMINISTRATION

- Recommended dosage of Beleodaq is 1,000 mg/m^2 administered over 30 minutes by intravenous infusion once daily on days 1 through 5 of a 21-day cycle. Cycles can be repeated until disease progression or unacceptable toxicity. (2.1)
- Treatment discontinuation or interruption with or without dosage reductions by 25% may be needed to manage adverse reactions (2.2)
- Reduce dosage in patients with moderate hepatic or renal impairment. (2.3, 2.4, 8.6, 8.7)
- Avoid use in patients with severe hepatic or renal impairment. (2.3, 2.4, 8.6, 8.7)
- Modify dosage in patients known to be homozygous for the UGT1A1*28 allele. (2.5)
- See the full prescribing information for preparation and administration instructions. (2.7)

3 DOSAGE FORMS AND STRENGTHS

For injection: 500 mg, lyophilized powder in single-dose vial for reconstitution (3)

4 CONTRAINDICATIONS

None. (4)

5 WARNINGS AND PRECAUTIONS

- Hematologic Toxicity: Thrombocytopenia, leukopenia (neutropenia and lymphopenia), and anemia: Monitor blood counts and modify dosage for hematologic toxicities. (2.2, 5.1)
- Infection: Serious and fatal infections (e.g., pneumonia and sepsis) (5.2)
- Hepatotoxicity: Beleodaq may cause hepatic toxicity and liver function test abnormalities. Monitor liver function tests and omit or modify dosage for hepatic toxicities. (2.2, 5.3)
- Tumor lysis syndrome: Monitor patients with advanced stage disease and/or high tumor burden and take appropriate precautions (5.4)
- Gastrointestinal Toxicity: Nausea, vomiting and diarrhea occur with Beleodaq and may require antiemetic and antidiarrheal medications (5.5).
- Embryo-Fetal Toxicity: Can cause fetal harm. (5.6)

6 ADVERSE REACTIONS

The most common adverse reactions (>25%) are nausea, fatigue, pyrexia, anemia, and vomiting. (6)

To report SUSPECTED ADVERSE REACTIONS, contact Acrotech Biopharma Inc at 1-888-292-9617 or FDA at 1-800-FDA-1088 or www.fda.gov/medwatch

7 DRUG INTERACTIONS

UGT1A1 Inhibitors: Avoid use or modify dosage if use is unavoidable. (2.6, 7.1)

8 USE IN SPECIFIC POPULATIONS

Lactation: Advised not to breastfeed. (8.2)

FULL PRESCRIBING INFORMATION

1 INDICATIONS AND USAGE

Beleodaq is indicated for the treatment of adult patients with relapsed or refractory peripheral T-cell lymphoma (PTCL).

This indication is approved under accelerated approval based on tumor response rate and duration of response [see Clinical Studies (14)]. An improvement in survival or disease-related symptoms has not been established. Continued approval for this indication may be contingent upon verification and description of clinical benefit in the confirmatory trial.

2 DOSAGE AND ADMINISTRATION

2.1 Recommended Dosage

The recommended dosage of Beleodaq is 1,000 mg/m^2 administered over 30 minutes by intravenous infusion once daily on Days 1 through 5 of a 21-day cycle. Cycles can be repeated every 21 days until disease progression or unacceptable toxicity.

2.2 Dosage Modification for Hematologic and Non-Hematologic Toxicities

Table 1 displays the recommended Beleodaq dosage modifications for hematologic and non-hematologic toxicities. Base dosage adjustments for thrombocytopenia and neutropenia on platelet and absolute neutrophil nadir (lowest value) counts in the preceding cycle of therapy.

- Absolute neutrophil count (ANC) should be greater than or equal to 1 x 10^9/L and the platelet count should be greater than or equal to 50 x 10^9/L prior to the start of each cycle and prior to resuming treatment following toxicity. Resume subsequent treatment with Beleodaq according to the guidelines described in Table 1 below. Discontinue Beleodaq in patients who have recurrent ANC nadirs less than 0.5 x 10^9/L and/or recurrent platelet count nadirs less than 25 x 10^9/L after two dosage reductions.
- Other toxicities must be NCI-CTCAE Grade 2 or less prior to re-treatment.

Monitor complete blood counts at baseline and weekly. Perform serum chemistry tests, including renal and hepatic functions prior to the start of the first dose of each cycle.

Table 1: Dosage Modifications for Hematologic and Non-Hematologic Toxicities
 | Dosage Modification
Dosage Modifications due to Hematologic Toxicities
Platelet count ≥ 25 x 10^9/L and nadir ANC ≥ 0.5 x 10^9/L | No Change
Nadir ANC < 0.5 x 10^9/L (any platelet count) | Decrease dosage by 25% (750 mg/m^2)
Platelet count < 25 x 10^9/L (any nadir ANC) | Decrease dosage by 25% (750 mg/m^2)
Dosage Modifications due to Non-Hematologic Toxicities
Any CTCAE Grade 3 or 4 adverse reactionª | Decrease dosage by 25% (750 mg/m^2)
Recurrence of CTCAE Grade 3 or 4 adverse reaction after two dosage reductions | Discontinue Beleodaq

ªFor nausea, vomiting, and diarrhea, dose modification may not be necessary if the duration is less than 7 days with supportive management

2.3 Recommended Dosage in Patients with Hepatic Impairment

Beleodaq dosage in patients with moderate hepatic impairment (total bilirubin > 1.5 to 3 x ULN, any aspartate aminotransferase (AST)) is 500 mg/m^2 administered over 30 minutes by intravenous infusion once daily on Days 1 through 5 of a 21-day cycle. Avoid use of Beleodaq in patients with severe hepatic impairment (total bilirubin > 3 x ULN, any AST). No dosage adjustment is recommended for patients with mild hepatic impairment (total bilirubin ≤ 1.5 x ULN, any AST). Hepatic impairment is defined per the National Cancer Institute Organ Dysfunction Working Group.

2.4 Recommended Dosage in Patients with Renal Impairment

Beleodaq dosage in patients with moderate renal impairment (creatinine clearance [CLcr] 30 to <60 mL/min) is 500 mg/m^2 administered over 30 minutes by intravenous infusion once daily on Days 1 through 5 of a 21-day cycle. Avoid use of Beleodaq in patients with severe renal impairment (CLcr < 30 mL/min). No dosage adjustment is recommended for patients with mild renal impairment (CLcr 60 to < 90 mL/min).

2.5 Dosage Modification for Patients with Reduced UGT1A1 Activity

Reduce the starting dose of Beleodaq to 750 mg/m^2 in patients known to be homozygous for the UGT1A1*28 allele [see Clinical Pharmacology (12.5)].

2.6 Dosage Modification for Concomitant Use with UGT1A1 Inhibitors

Avoid concomitant use of Beleodaq with UGT1A1 inhibitors. If concomitant use of a UGT1A1 inhibitor is unavoidable, reduce the Beleodaq dosage by 25% as shown in Table 2.

Table 2: Dosage Modifications for Concomitant Use with a UGT1A1 Inhibitor
Beleodaq Starting Dosage | Beleodaq Modified Dosage
1,000 mg/m^2 | 750 mg/m^2
750 mg/m^2 | 562.5 mg/m^2
500 mg/m^2 | Interrupt Beleodaq treatment for the duration of UGT1A1 inhibitor use. After discontinuation of a UGT1A1 inhibitor of 5 half-lives, resume the Beleodaq dosage that was taken prior to initiating the UGT1A1 inhibitor.

2.7 Preparation and Administration

Beleodaq is a hazardous drug. Follow applicable special handling and disposal procedures.^1

Preparation:

- Aseptically reconstitute each vial of Beleodaq by adding 9 mL of Sterile Water for Injection into the Beleodaq vial with a suitable syringe to achieve a concentration of 50 mg of belinostat per mL. Swirl the contents of the vial until there are no visible particles in the resulting solution. If not used immediately, the reconstituted product may be stored for up to 12 hours at room temperature (15°C to 25°C; 59°F to 77°F).
- Aseptically withdraw the volume needed for the required dosage (based on the 50 mg/mL concentration and the patient’s BSA [m^2]) and transfer to an infusion bag containing 250 mL of 0.9 % Sodium Chloride Injection. If not used immediately, the infusion bag with drug solution may be stored at room temperature (15°C to 25°C; 59°F to 77°F) for up to 36 hours including infusion time.
- Visually inspect the solution for particulate matter. Do not use if cloudiness or particulates are observed.

Administration:

- Connect the infusion bag containing drug solution to an infusion set with a 0.22 micron in-line filter for administration.
- Infuse intravenously over 30 minutes. If infusion site pain or other symptoms potentially attributable to the infusion occur, the infusion time may be extended to 45 minutes.

3 DOSAGE FORMS AND STRENGTHS

For injection: 500 mg, lyophilized powder in single-dose vial for reconstitution

4 CONTRAINDICATIONS

None

5 WARNINGS AND PRECAUTIONS

5.1 Hematologic Toxicity

Beleodaq can cause thrombocytopenia, leukopenia (neutropenia and lymphopenia), and/or anemia; monitor blood counts weekly during treatment, and modify dosage as necessary [see Dosage and Administration (2.2) and Adverse Reactions(6.1)].

5.2 Infections

Serious and sometimes fatal infections, including pneumonia and sepsis, have occurred with Beleodaq. Do not administer Beleodaq to patients with an active infection. Patients with a history of extensive or intensive chemotherapy may be at higher risk of life threatening infections [see Adverse Reactions (6.1)].

5.3 Hepatotoxicity

Beleodaq can cause fatal hepatotoxicity and liver function test abnormalities [see Adverse Reactions (6.1)]. Monitor liver function tests before treatment and before the start of each cycle. Interrupt or adjust dosage until recovery, or permanently discontinue Beleodaq based on the severity of the hepatic toxicity[see Dosage and Administration (2.2) and Clinical Pharmacology (12.3)].

5.4 Tumor Lysis Syndrome

Tumor lysis syndrome has occurred in Beleodaq-treated patients in the clinical trial of patients with relapsed or refractory PTCL [see Clinical Studies (14)]. Monitor patients with advanced stage disease and/or high tumor burden and take appropriate precautions [see Adverse Reactions (6.1)].

5.5 Gastrointestinal Toxicity

Nausea, vomiting and diarrhea occur with Beleodaq [see Adverse Reactions (6.1)] and may require the use of antiemetic and antidiarrheal medications.

5.6 Embryo-fetal Toxicity

Based on its mechanism of action and findings of genotoxicity, Beleodaq can cause fetal harm when administered to a pregnant woman [see Clinical Pharmacology (12.1) and Nonclinical Toxicology (13.1)]. Advise pregnant women of the risk to a fetus. Advise females of reproductive potential to use an effective method of contraception during treatment with Beleodaq and for 6 months after the last dose [see Use in Specific Populations (8.1, 8.3). Advise males with female partners of reproductive potential to use effective contraception during treatment with Beleodaq and for 3 months after the last dose.

6 ADVERSE REACTIONS

The following clinically significant adverse reactions are described in more detail in other sections of the prescribing information.

- Hematologic Toxicity [see Warnings and Precautions (5.1)]
- Infection [see Warnings and Precautions (5.2)]
- Hepatotoxicity [see Warnings and Precautions (5.3)]
- Tumor Lysis Syndrome [see Warnings and Precautions (5.4)]
- Gastrointestinal Toxicity [see Warnings and Precautions (5.5)]

6.1 Clinical Trials Experience

Because clinical trials are conducted under widely varying conditions, adverse reaction rates observed in the clinical trials of Beleodaq may not reflect the rates observed in practice.

Adverse Reactions in Patients with Peripheral T-Cell Lymphoma

The safety of Beleodaq was evaluated in 129 patients with relapsed or refractory PTCL in the single arm clinical trial in which patients were administered Beleodaq at a dosage of 1,000 mg/m^2 administered over 30 minutes by IV infusion once daily on Days 1 through 5 of a 21-day cycle [see Clinical Studies (14)]. The median duration of treatment was 2 cycles (range 1 – 33 cycles).

The most common adverse reactions observed in the trial of patients with relapsed or refractory PTCL treated with Beleodaq were nausea, fatigue, pyrexia, anemia, and vomiting [see Clinical Studies (14)]. Table 3 summarizes the adverse reactions regardless of causality from the trial in patients with relapsed or refractory PTCL.

Table 3: Adverse Reactions Occurring in ≥ 10% of Patients with Relapsed or Refractory PTCL (NCI CTC Grade 1-4)
Adverse Reactions | Percentage of Patients (%) (N=129)
 | All Grades | Grade 3 or 4
All Adverse Reactions | 97 | 61
Nausea | 42 | 1
Fatigue | 37 | 5
Pyrexia | 35 | 2
Anemia | 32 | 11
Vomiting | 29 | 1
Constipation | 23 | 1
Diarrhea | 23 | 2
Dyspnea | 22 | 6
Rash | 20 | 1
Peripheral Edema | 20 | 0
Cough | 19 | 0
Thrombocytopenia | 16 | 7
Pruritus | 16 | 3
Chills | 16 | 1
Increased Blood Lactate Dehydrogenase | 16 | 2
Decreased Appetite | 15 | 2
Headache | 15 | 0
Infusion Site Pain | 14 | 0
Hypokalemia | 12 | 4
Prolonged QT | 11 | 4
Abdominal pain | 11 | 1
Hypotension | 10 | 3
Phlebitis | 10 | 1
Dizziness | 10 | 0

Note: Adverse reactions are listed by order of incidence in the “All Grades” category first, then by incidence in “the Grade 3 or 4” category; Measured by National Cancer Institute Common Terminology Criteria for Adverse Events (NCI-CTCAE) version 3.0

Serious Adverse Reactions

Sixty-one patients (47.3%) experienced serious adverse reactions while taking Beleodaq or within 30 days after their last dose of Beleodaq. The most common serious adverse reactions (> 2%) were pneumonia, pyrexia, infection, anemia, increased creatinine, thrombocytopenia, and multi-organ failure. One treatment-related death associated with hepatic failure was reported in the trial.

One patient with baseline hyperuricemia and bulky disease experienced Grade 4 tumor lysis syndrome during the first cycle of treatment and died due to multi-organ failure. A treatment-related death from ventricular fibrillation was reported in another monotherapy clinical trial with Beleodaq. ECG analysis did not identify QTc prolongation.

Discontinuations due to Adverse Reactions

Twenty-five patients (19.4%) discontinued treatment with Beleodaq due to adverse reactions. The adverse reactions reported most frequently as the reason for discontinuation of treatment included anemia, febrile neutropenia, fatigue, and multi-organ failure.

Dosage Modifications due to Adverse Reactions

In the trial, dosage adjustments due to adverse reactions occurred in 12% of Beleodaq-treated patients.

7 DRUG INTERACTIONS

7.1 UGT1A1 Inhibitors

Avoid concomitant administration of Beleodaq with UGT1A1inhibitors. If concomitant use of a UGT1A1 inhibitor is unavoidable, modify the Beleodaq dose [see Dosage and Administration (2.6)].
Belinostat is primarily metabolized by UGT1A1. Concomitant use with a UGT1A1 inhibitor increases belinostat exposure [see Clinical Pharmacology (12.3)], which may increase the risk of Beleodaq adverse reactions.

8 USE IN SPECIFIC POPULATIONS

8.1 Pregnancy

Risk Summary

Based on its mechanism of action, Beleodaq can cause teratogenicity and/or embryo-fetal lethality because it is genotoxic and targets actively dividing cells [see Clinical Pharmacology (12.1) and Nonclinical Toxicology (13.1)]. There are no available data on Beleodaq use in pregnant women to evaluate for a drug-associated risk of major birth defects, miscarriage or adverse maternal or fetal outcomes. No animal reproduction studies were conducted with Beleodaq. Advise pregnant women of the potential risk to a fetus.

The estimated background risk of major birth defects and miscarriage for the indicated population(s) is unknown. All pregnancies have a background risk of birth defect, loss, or other adverse outcomes. In the U.S. general population, the estimated background risk of major birth defects and miscarriage in clinically recognized pregnancies is 2-4% and 15-20%, respectively.

8.2 Lactation

Risk Summary

There are no data on the presence of belinostat in human milk, the effects on the breastfed child, or the effects on milk production. Because of the potential for serious adverse reactions in the breastfed child, advise patients that breastfeeding is not recommended during treatment with Beleodaq, and for 2 weeks after the last dose

8.3 Females and Males of Reproductive Potential

Beleodaq can cause embryo-fetal harm when administered to a pregnant woman [see Use in Specific Populations (8.1)].
Pregnancy Testing
Pregnancy testing is recommended for females of reproductive potential prior to initiating Beleodaq.
Contraception
Females
Advise females of reproductive potential to use effective contraception during treatment with Beleodaq and for 6 months after the last dose.
Males
Based on genotoxicity findings, advise males with female partners of reproductive potential to use effective contraception during treatment with Beleodaq and for 3 months after the last dose [see Nonclinical Toxicology (13.1)].
Infertility
Males
Based on findings from animal studies, Beleodaq may impair male fertility. The reversibility of the effect on fertility is unknown [see Nonclinical Toxicology (13.1)].

8.4 Pediatric Use

The safety and effectiveness of Beleodaq in pediatric patients have not been established.

8.5 Geriatric Use

In the single-arm trial, 48% of patients (N = 62) were ≥ 65 years of age and 10% of patients (N=13) were ≥ 75 years of age [see Clinical Studies (14)]. The median age of the trial population was 63 years. Patients ≥ 65 years of age had a higher response rate to Beleodaq treatment than patients < 65 years of age (36% versus 16%) while no meaningful differences in response rate were observed between patients ≥ 75 years of age and those < 75 years of age. No clinically meaningful differences in serious adverse reactions were observed in patients based on age (< 65 years compared with ≥ 65 years or < 75 years of age compared with ≥ 75 years of age).

8.6 Use in Patients with Hepatic Impairment

No dosage adjustment is recommended for patients with mild hepatic impairment (total bilirubin ≤ 1.5 x ULN, any AST). Reduce the Beleodaq dosage in patients with moderate hepatic impairment (total bilirubin > 1.5 to 3 x ULN, any AST) [see Dosage and Administration (2.3)]. Avoid use of Beleodaq in patients with severe hepatic impairment (total bilirubin > 3 x ULN, any AST) [see Clinical Pharmacology (12.3)].

Belinostat is metabolized in the liver, moderate hepatic impairment (total bilirubin > 1.5 to 3 x ULN, any AST) and severe hepatic impairment (total bilirubin > 3 x ULN, any AST) increases belinostat exposure [see Clinical Pharmacology (12.3)], which may increase the risk of Beleodaq adverse reactions.

8.7 Use in Patients with Renal Impairment

No dosage adjustment is recommended for patients with mild renal impairment (CLcr 60 to < 90 mL/min). Reduce the Beleodaq dosage in patients with moderate renal impairment (CLcr 30 to <60 mL/min) [see Dosage and Administration (2.4)]. Avoid use of Beleodaq in patients with severe renal impairment (CLcr < 30 mL/min).

Moderate renal impairment (CLcr 30 to <60 mL/min) increases belinostat exposure [see Clinical Pharmacology (12.3)], which may increase the risk of Beleodaq adverse reactions. The effect of severe renal impairment (CLcr < 30 mL/min) on belinostat pharmacokinetics is unknown [see Clinical Pharmacology (12.3)].

10 OVERDOSAGE

No specific information is available on the treatment of overdosage of Beleodaq. There is no antidote for Beleodaq and it is not known if Beleodaq is dialyzable. If an overdose occurs, general supportive measures should be instituted as deemed necessary by the treating physician. The elimination half-life of belinostat is 1.1 hours [see Clinical Pharmacology (12.3)].

11 DESCRIPTION

Beleodaq is a histone deacetylase inhibitor with a sulfonamide-hydroxamide structure. The chemical name of belinostat is (2E)-N-hydroxy-3-[3-(phenylsulfamoyl)phenyl]prop-2-enamide. The structural formula is as follows:

The molecular formula is C15H14N2O4S and the molecular weight is 318.35 g/mol.

Belinostat is a white to off-white powder. It is slightly soluble in distilled water (0.14 mg/mL) and polyethylene glycol 400 (about 1.5 mg/mL), and is freely soluble in ethanol (> 200 mg/mL). The pKa values are 7.87 and 8.71 by potentiometry and 7.86 and 8.59 by UV.

Beleodaq (belinostat) for injection is supplied as a sterile lyophilized yellow powder containing 500 mg belinostat as the active ingredient. Each vial also contains 1000 mg L-Arginine, USP as an inactive ingredient. The drug product is supplied in a single-dose clear glass vial with a coated stopper and aluminum crimp seal with “flip-off” cap. Beleodaq is intended for intravenous administration after reconstitution with 9 mL Sterile Water for injection, and the reconstituted solution is further diluted with 250 mL of sterile 0.9% Sodium Chloride injection prior to infusion [see Dosage and Administration (2)].

12 CLINICAL PHARMACOLOGY

12.1 Mechanism of Action

Beleodaq is a histone deacetylase (HDAC) inhibitor. HDACs catalyze the removal of acetyl groups from the lysine residues of histones and some non-histone proteins. In vitro, belinostat caused the accumulation of acetylated histones and other proteins, inducing cell cycle arrest and/or apoptosis of some transformed cells. Belinostat shows preferential cytotoxicity towards tumor cells compared to normal cells. Belinostat inhibited the enzymatic activity of histone deacetylases at nanomolar concentrations (<250 nM).

12.2 Pharmacodynamics

Belinostat exposure-response relationships and the time course of pharmacodynamic response are not fully characterized.

Cardiac Electrophysiology

Multiple clinical trials have been conducted with Beleodaq, in many of which ECG data were collected and analyzed by a central laboratory. Analysis of clinical ECG and belinostat plasma concentration data demonstrated no meaningful effect of Beleodaq on cardiac repolarization. None of the trials showed any clinically relevant changes caused by Beleodaq on heart rate, PR duration or QRS duration as measures of autonomic state, atrio-ventricular conduction or depolarization; there were no cases of Torsades de Pointes.

12.3 Pharmacokinetics

The pharmacokinetic characteristics of belinostat were analyzed from pooled data from phase 1/2 clinical studies that used doses of belinostat ranging from 150 to 1200 mg/m^2 (0.15 to 1.2 times the approved recommended dosage).

Distribution
The mean belinostat volume of distribution approaches total body water, indicating that belinostat has limited body tissue distribution. In vitro plasma studies have shown that between 92.9% and 95.8% of belinostat is bound to protein in an equilibrium dialysis assay, and was independent of belinostat plasma concentrations from 500 to 25,000 ng/mL.

Elimination
Belinostat elimination half-life is 1.1 hours with a total mean plasma clearance of 1240 mL/min. The total clearance approximates average hepatic blood flow (1500 mL/min), suggesting high hepatic extraction (clearance being flow dependent).

Metabolism
Belinostat is primarily metabolized by hepatic UGT1A1. Belinostat also undergoes hepatic metabolism by CYP2A6, CYP2C9, and CYP3A4 enzymes.

Excretion
Following a single dose of radiolabeled belinostat (100 μCi, 1500 mg) administered as a 30-minute intravenous infusion in patients with recurrent or progressive malignancy, fecal excretion accounted for a mean (± SD) of 9.7% (± 6.5%) of the administered radioactive belinostat dose over 168 hours. The mean (± SD) of the administered radioactive belinostat dose that was excreted in urine over 168 hours was 84.8% (± 9.8%), of which unchanged belinostat accounted for only 1.7%.

Specific Populations
Hepatic Impairment
Belinostat steady state clearance decreased and AUC increased as a function of the degree of liver dysfunction, but were unchanged for Cmax, half‐life and apparent volume of distribution. Mean belinostat clearance was reduced by 18% in mild (total bilirubin ≤ ULN and AST >ULN, or total bilirubin ˃1 to 1.5 x ULN), 24% in moderate (total bilirubin ˃ 1.5 to 3 times ULN and any value for AST) and 33% in severe hepatic impairment (total bilirubin ˃ 3 to 10 times ULN and any value for AST). Increases in belinostat exposure were correlated with worsening liver function, but there was no obvious relationship between exposure and DLTs during the first cycle of therapy.

Renal Impairment
Belinostat Cmax increased by 1.7-fold, AUC0-∞ by 1.3-fold and CLtot was unchanged in patients with mild renal impairment (CLcr 60 to <90 ml/min). Belinostat Cmax and AUC0-∞ increased by 1.7-fold and CLtot decreased by 26% in patients with moderate renal impairment (CLcr 30 < 60 ml/min). The effect of severe renal impairment (CLcr < 30 mL/min) on belinostat pharmacokinetics is unknown.

Drug Interaction Studies
Clinical Studies and Model-Informed Approaches
UGT1A1 inhibitors: Belinostat t1/2 increased by 1.5-fold, AUC0-inf increased by 1.4-fold, Cmax decreased by 33%, and renal excretion increased by 2.5-fold following concomitant administration with atazanavir (UGT1A1 inhibitor), but there was minimal change in steady state clearance. There was minimal change in belinostat glucuronide Cmax, AUC0-24; however, belinostat glucuronide excretion decreased by 48%.

Warfarin: No clinically significant differences in the pharmacokinetics of R- or S-warfarin were observed when used concomitantly with belinostat.

In Vitro Studies
CYP450 Enzymes: Belinostat and its metabolites are CYP2C8 and CYP2C9 inhibitors.

Transporter Systems: Belinostat is a glycoprotein (P-gp) substrate but is not a P-gp inhibitor.

12.5 Pharmacogenomics

UGT1A1 activity is reduced in individuals with genetic polymorphisms that lead to reduced enzyme activity such as the UGT1A1*28 polymorphism. Approximately 20% of the Black population, 10% of the White population, and 2% of the Asian population are homozygous for the UGT1A1*28 allele. Additional reduced function alleles may be more prevalent in specific populations.

Because belinostat is primarily (80 -90%) metabolized by UGT1A1, the clearance of belinostat could be decreased in patients with reduced UGT1A1 activity (e.g., patients with UGT1A1*28 allele). Reduce the starting dose of Beleodaq to 750 mg/m^2 in patients known to be homozygous for the UGT1A1*28 allele to minimize dose limiting toxicities. [see Dosage and Administration (2.5)].

13 NONCLINICAL TOXICOLOGY

13.1 Carcinogenesis, Mutagenesis, Impairment of Fertility

Carcinogenicity studies have not been performed with belinostat.

Belinostat was genotoxic in a bacterial reverse mutation test (AMES assay), an in vitro mouse lymphoma cell mutagenesis assay, and an in vivo rat micronucleus assay.

Beleodaq may impair male fertility. Fertility studies using belinostat were not conducted. However, belinostat effects on male reproductive organs observed during the 24-week repeat-dose dog toxicology study included reduced organ weights of the testes/epididymides that correlated with a delay in testicular maturation.

14 CLINICAL STUDIES

Relapsed or Refractory Peripheral T-cell Lymphoma (PTCL)

In an open-label, single-arm, non-randomized international trial conducted at 62 centers, 129 patients with relapsed or refractory PTCL were treated with Beleodaq 1,000 mg/m^2 administered over 30 minutes via IV infusion once daily on Days 1 through 5 of a 21-day cycle. There were 120 patients who had histologically confirmed PTCL by central review evaluable for efficacy. Patients were treated with repeat cycles every three weeks until disease progression or unacceptable toxicity.

Efficacy was evaluated using response rate (complete response and partial response) as assessed by an independent review committee (IRC) using the International Workshop Criteria (IWC) (Cheson 2007). Response assessments were evaluated every 6 weeks for the first 12 months and then every 12 weeks until 2 years from the start of study treatment. Duration of response was measured from the first day of documented response to disease progression or death. Response and progression of disease were evaluated by the IRC using the IWC.

Table 4 summarizes the baseline demographic and disease characteristics of the study population, who were evaluable for efficacy.

Table 4 Baseline Patient Characteristics (PTCL Population)
Characteristics | Evaluable Patients (N=120)
Age (years) Median (range) | 64 (29-81)
Sex, % Male Female | 52 48
Race, % White Black Asian Latin Other | 88 6 3 3 2
PTCL Subtype Based on Central Diagnosis, % PTCL Unspecified (NOS) Angioimmunoblastic T-cell lymphoma (AITL) ALK-1 negative anaplastic large cell lymphoma (ALCL) Other | 64 18 11 7
Baseline Platelet Count, % ≥100,000/μL <100,000/μL | 83 17
ECOG Performance Status, % 0 1 2 3 | 34 43 22 1
Median Time (months) from Initial PTCL Diagnosis (Range) | 12 (2.6 - 266.4)
Median Number of Prior Systemic Therapies (Range) | 2 (1-8)

In all evaluable patients (N = 120) treated with Beleodaq, the overall response rate per central review using IWC was 25.8% (N = 31) (Table 5) with rates of 23.4% for PTCL, NOS and 45.5% for AITL, the two largest subtypes enrolled.

Table 5: Response Analysis per Central Assessment Using IWC in Patients with Relapsed or Refractory PTCL
 | Evaluable Patients (N=120)
Response Rate | N (%) | (95% CI)
CR+PR | 31 (25.8) | 18.3-34.6
CR | 13 (10.8) | 5.9-17.8
PR | 18 (15.0) | 9.1-22.7

CI=confidence interval, CR=complete response, PR=partial response

The median duration of response based on the first date of response to disease progression or death was 8.4 months (95% CI: 4.5 - 29.4). Of the responders, the median time to response was 5.6 weeks (range 4.3 - 50.4 weeks). Nine patients (7.5%) were able to proceed to a stem cell transplant after treatment with Beleodaq.

15 REFERENCES

^1 OSHA Hazardous Drugs. OSHA. http://www.osha.gov/SLTC/hazardousdrugs/index.html

16 HOW SUPPLIED/STORAGE AND HANDLING

How Supplied
Beleodaq (belinostat) for injection is supplied in single vial cartons; each clear vial contains sterile, lyophilized powder equivalent to 500 mg belinostat.
NDC 72893-002-01: Individual carton of Beleodaq single-dose vial containing 500 mg belinostat.

Storage and Handling

Store Beleodaq (belinostat) for injection at room temperature 20°C to 25°C (68°F to 77°F). Excursions are permitted between 15°C and 30°C (59°F and 86°F). Retain in original package until use. [see USP Controlled Room Temperature].
Beleodaq is a hazardous drug.Follow special handling and disposal procedures.^1

17 PATIENT COUNSELING INFORMATION

Physicians should discuss the FDA approved Patient Information Leaflet with patients prior to treatment with Beleodaq. Instruct patients to read the Patient Information Leaflet carefully.
Advise the patient or the caregiver to read the FDA-approved patient labeling (Patient Information).
Advise patients or their caregivers:

- To report symptoms of nausea, vomiting and diarrhea so that appropriate antiemetic and antidiarrheal medications can be administered [see Warnings and Precautions (5.5) ].

- To report any symptoms of thrombocytopenia, leukopenia (neutropenia and lymphopenia), and anemia [see Warnings and Precautions (5.1) ].

- To immediately report symptoms of infection (e.g., pyrexia) [see Warnings and Precautions (5.2) and Adverse Reactions (6.1) ].

- Of the potential risk to the fetus and for women to avoid pregnancy and use effective contraception while receiving Beleodaq and for 6 months after the last dose [see Warnings and Precautions (5.6)]. Advise males with female partners of reproductive potential to use effective contraception during treatment with Beleodaq and for 3 months after the last dose.

- To avoid breastfeeding while receiving Beleodaq and for 2 weeks after the last dose [see Use in Specific Populations (8.2) ].

- To understand the importance of monitoring liver function test abnormalities and to immediately report potential symptoms of liver injury [see Dosage and Administration (2.2) and Warnings and Precautions (5.3) ].

Manufactured by:
Cenexi Laboratories Thissen SA
Braine I'Alleud, 1420, Belgium
Manufactured for:
Acrotech Biopharma Inc
East Windsor, NJ 08520 USA
Beleodaq is a registered trademark of Acrotech Biopharma Inc. All rights are reserved.
U.S. Patent: 6,888,027

SPL PATIENT PACKAGE INSERT SECTION

PATIENT INFORMATION
BELEODAQ®(Bē-lēo-dak)
(belinostat) for injection, for intravenous use

Read this Patient Information before you receive treatment with Beleodaq and each time you receive Beleodaq. There may be new information. This leaflet does not take the place of talking to your doctor about your medical condition or your treatment.

What is Beleodaq?
Beleodaq is a prescription medicine used to treat people with a type of cancer called peripheral T-cell Lymphoma (PTCL) that comes back or does not respond to cancer treatment.
It is not known if Beleodaq is safe and effective in children.

What should I tell my doctor before receiving Beleodaq?
Before receiving Beleodaq, tell your doctor about all of your medical conditions, including if you:

- have an infection
- have had chemotherapy treatment
- have liver or kidney problems
- have nausea, vomiting, or diarrhea
- are pregnant or plan to become pregnant. Beleodaq can harm your unborn baby. You should not become pregnant while receiving Beleodaq. Tell your doctor right away if you become pregnant while receiving Beleodaq.
- are breastfeeding or plan to breastfeed. It is not known if Beleodaq passes into your breast milk. You and your doctor should decide if you will receive Beleodaq or breastfeed. You should not do both.

Tell your doctor about all the medicines you take, including prescription and over-the-counter medicines, vitamins, and herbal supplements.

How will I receive Beleodaq?

- Beleodaq will be given to you by intravenous (IV) injection into your vein, usually over 30 minutes.
- Beleodaq is given one time a day on Days 1 through 5 of a 21-day cycle of treatment.
- You should have regular blood tests before and during your treatment with Beleodaq.
- Your doctor may change your dose of Beleodaq, change when you receive your treatment, or stop treatment if you have certain side effects while receiving Beleodaq.

What are the possible side effects of Beleodaq?
Beleodaq may cause serious side effects, including:
• Low blood cell counts. Your doctor will do blood tests to check your blood counts during your treatment with Beleodaq.
o Low platelet counts can cause unusual bleeding or bruising under your skin.
o Low red blood cell counts may make you feel weak, tired, or you get tired easily, you look pale, or you feel short of breath.
o Low white blood cell counts can cause you to get infections, which may be serious.
• Serious infections. People receiving Beleodaq may develop serious infections that can sometimes lead to death. You may have a greater risk of life-threatening infections if you have had chemotherapy in the past. Tell your doctor right away if you have any of the following signs or symptoms of an infection: fever, flu-like symptoms, cough, shortness of breath, burning with urination, muscle aches, or worsening skin problems.
• Liver problems. Beleodaq may cause liver problems which can lead to death. Your doctor will do blood tests during your treatment with Beleodaq to check for liver problems. Tell your doctor right away if you have any of the following signs or symptoms of liver problems: yellowing of the skin or the white part of your eyes (jaundice), dark urine, itching, or pain in the right upper stomach area.
• Tumor Lysis Syndrome (TLS). TLS is caused by a fast breakdown of cancer cells. Your doctor will check you for TLS during treatment with Beleodaq.
• Nausea, vomiting, and diarrhea are common with Beleodaq and can sometimes be serious. Tell your doctor if you develop nausea, vomiting or diarrhea. Your doctor may prescribe medicines to help prevent or treat these side effects.
Common side effects of Beleodaq include fatigue, fever, and low red blood cell count. Tell your doctor if you have any side effect that bothers you or that does not go away.
These are not all the possible side effects of Beleodaq. Call your doctor for medical advice about side effects. You can report side effects to FDA at 1-800-FDA-1088.

General information about Beleodaq
Medicines are sometimes prescribed for purposes other than those listed in a Patient Information leaflet. You can ask your pharmacist or doctor for information about Beleodaq that is written for health professionals.

What are the ingredients in Beleodaq?
Active ingredient: belinostat
Inactive ingredients: L-Arginine
Manufactured by: Cenexi Laboratories Thissen SA, Braine I'Alleud, 1420, Belgium
Manufactured for: Acrotech Biopharma Inc, East Windsor, NJ 08520 USA
Beleodaq is a registered trademark of Acrotech Biopharma Inc. All rights reserved.
For more information, go to www.Beleodaq.com or call 1-888-292-9617.

This Patient Information has been approved by the U.S. Food and Drug Administration. Revised: Apr 2025

PACKAGE/LABEL PRINCIPAL DISPLAY PANEL

Carton Label

NDC 72893-002-01

Beleodaq® (belinostat) for injection

500 mg/vial

For Intravenous Infusion Only

Single-Dose Vial

Vial Label

NDC 72893-002-01
Beleodaq® (belinostat) for injection

500 mg/vial

For Intravenous Infusion Only

Single-Dose Vial